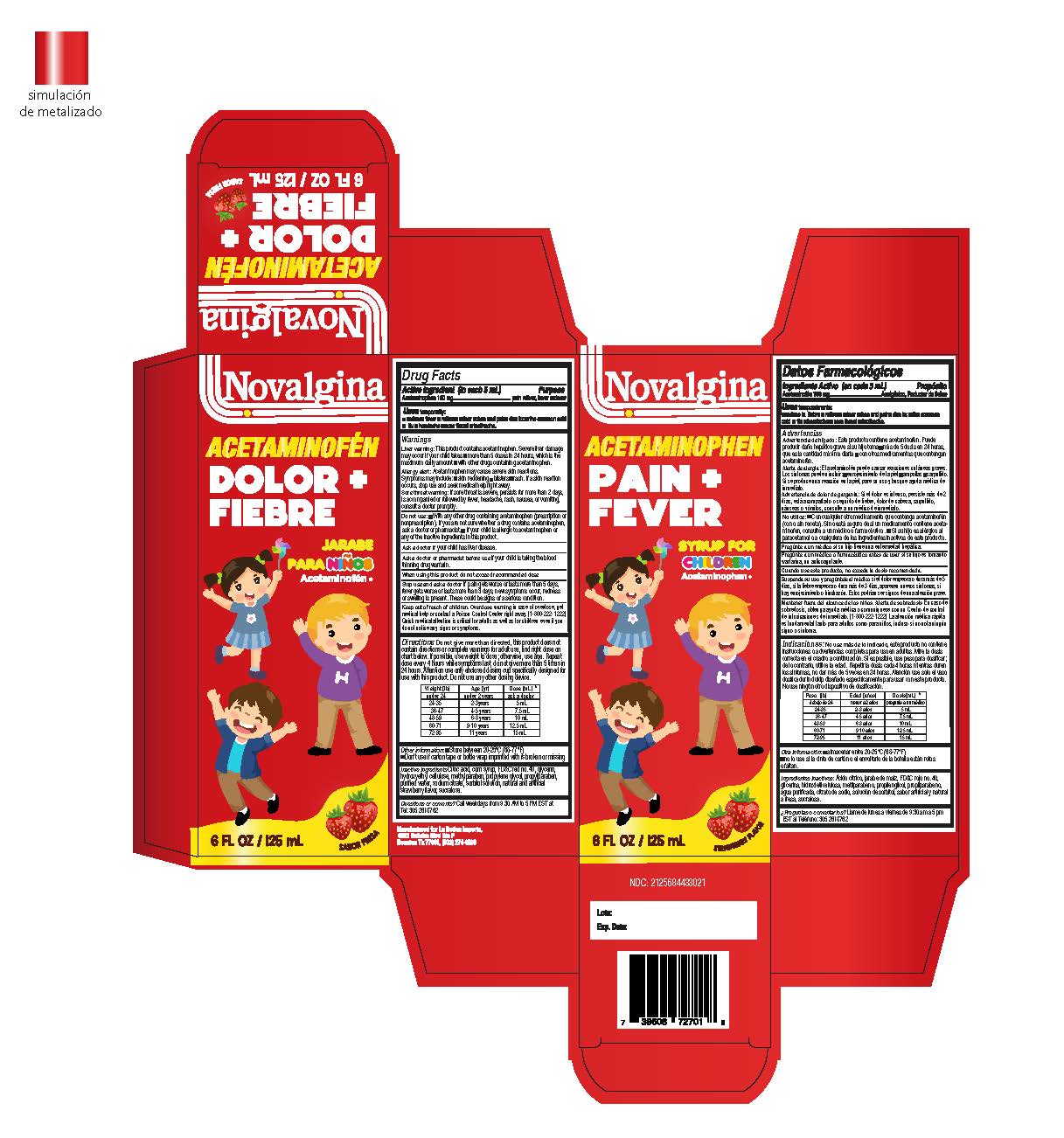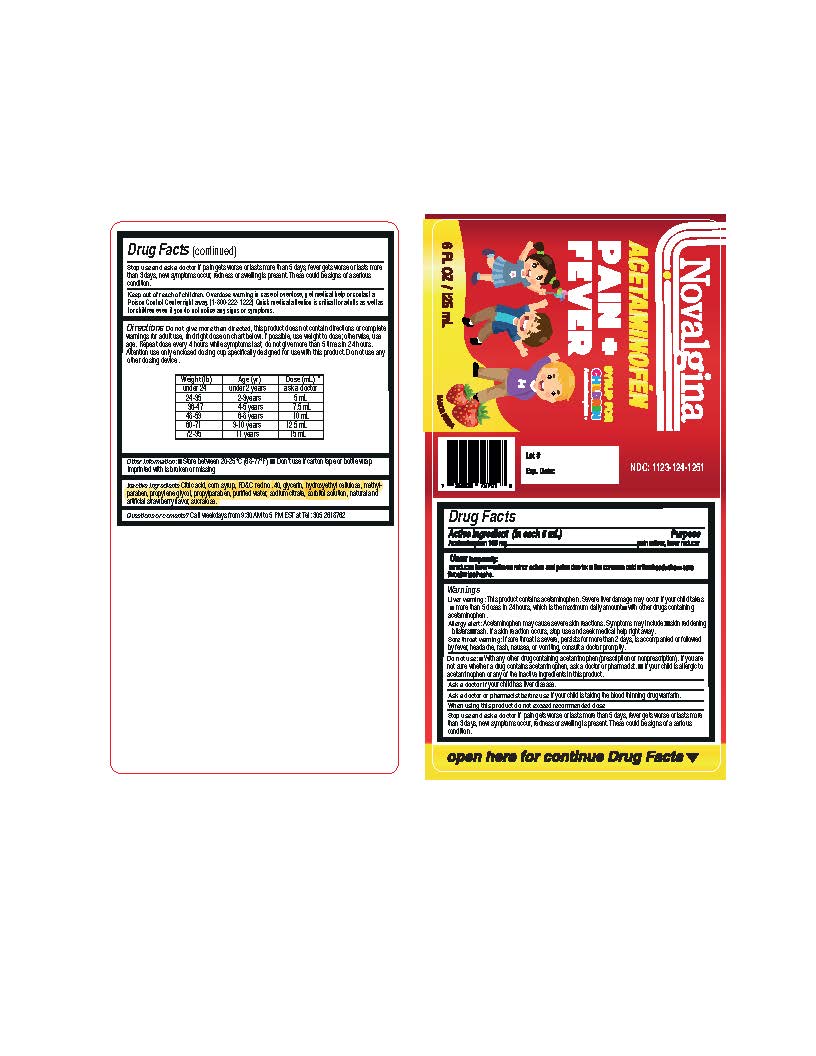 DRUG LABEL: Novalgina Acetaminophen Pain and Fever for Childrens
NDC: 83057-0003 | Form: SUSPENSION
Manufacturer: HBC Pharma, LLC
Category: otc | Type: HUMAN OTC DRUG LABEL
Date: 20241104

ACTIVE INGREDIENTS: ACETAMINOPHEN 160 mg/5 mL
INACTIVE INGREDIENTS: CORN SYRUP; CITRIC ACID MONOHYDRATE; WATER; SUCRALOSE; SORBITOL; PROPYLENE GLYCOL; SODIUM CITRATE; FD&C RED NO. 40; HYDROXYETHYL CELLULOSE (100 MPA.S AT 2%); GLYCERIN; METHYLPARABEN; PROPYLPARABEN

Novalgina Acetaminophen Pain and Fever for Children's

Active Ingredient

Acetaminophen, 160mg

Purpose

Pain reliever/fever reducer

Uses

temporarily:

■ reduces fever

■ relieves minor aches and pains due to: ■ the common cold ■ flu ■ headache ■ sore throat ■ toothache

Warnings

Liver Warning: This product contains acetaminophen. Severe liver damage may occur if your child takes ■ more than 5 doses in 24 hours, which is the maximum daily amount for this product

■ with other drugs containing acetaminophen.

Allergy alert: acetaminophen may cause severe skin reactions. Symptoms may include:

■ skin reddening ■ blisters ■ rash. If a skin reaction occurs, stop use and seek medical help right away

Sore throat warning: if sore throat is severe, persistent for more than 2 days, is accompanied or followed by fever, headache, rash, nausea, or vomiting. Consult a doctor promptly.

Do not use

- With any other drug containing acetaminophen (prescription or nonprescription). If you are not sure whether a drug contains acetaminophen, ask a doctor or pharmacist.
- If your child is allergic to acetaminophen or any of the inactive ingredients in this product.

Ask a doctor before use if your child

has liver disease

Ask a doctor or pharmacist before use if your

child is taking the blood thinning drug warfarin

Stop use and ask a doctor if

■ pain gets worse or lasts more than 5 days ■ fever gets worse or lasts more than 3 days ■ new symptoms occur ■ redness or swelling is present. These could be signs of a serious condition.

Keep out of reach of children.

Overdose warning in case of overdose, get medical help or contact a Poison Control Center right away. (1-800-222- 1222)
Quick medical attention is critical for adults as well as for children even if you do not notice any signs or symptoms.

Overdose warning

In case of overdose, get medical help or contact a Poison Control Center right away. (1-800-222- 1222) Quick medical attention is critical for adults as well as for children even if you do not notice any signs or symptoms.

Directions

Do not give more than directed, this product does not contain directions or complete warnings for adult use, find right dose on
chart below. If possible, use weight to dose; otherwise, use age. Repeat dose every 4 hours while symptoms last, do not give more than 5 times in 24 hours. Attention use only enclosed dosing cup specifically designed for use with this product. Do not use any other dosing device.

Weight (lbs) | Age (Years) | Dose
under 24 lbs. | under 2 years | Ask a doctor
24-35 lbs. | 2 - 3 years | 5 mL
36-47 lbs. | 4-5 years | 7.5
48-59 lbs. | 6-10 Years | 10 mL
60-71 lbs | 9-10 years | 12.5 mL
72-95 lbs | 11 years | 15 ml

Other Information

■ Store between 20-25°C (68-77°F)

■ Don’t use if carton tape or bottle wrap imprinted with is broken or missing

Inactive Ingredient

Citric acid, corn syrup, FD&C red no. 40, glycerin, hydroxyethyl cellulose, methylparaben, propylene glycol, propylparaben,
purified water, sodium citrate, sorbitol solution, natural and artificial strawberry flavor, sucralose.

Questions or Comments?

Call weekdays from 9:30 AM to 5 PM EST at Tel: 305 2618762